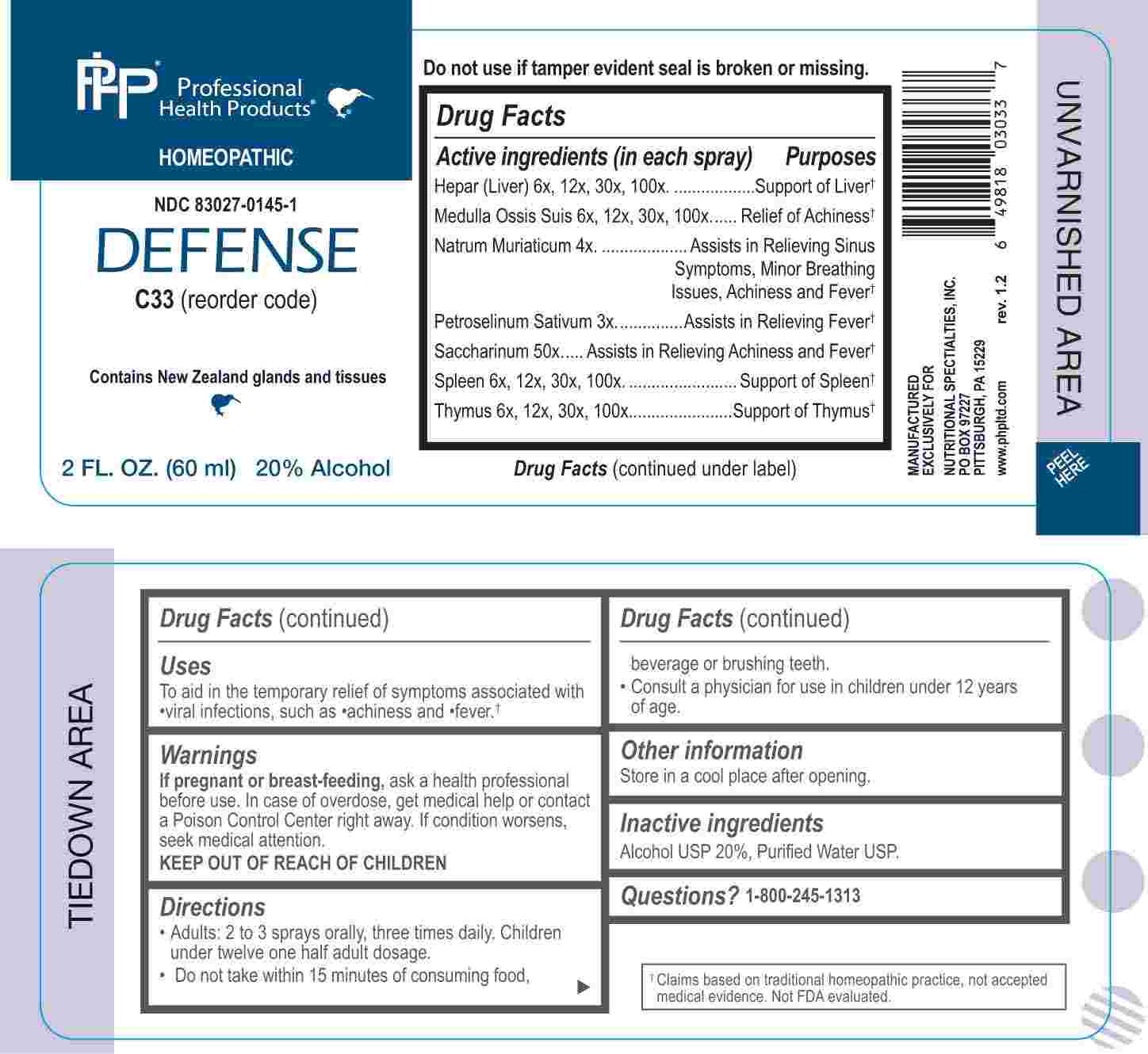 DRUG LABEL: Defense
NDC: 83027-0145 | Form: SPRAY
Manufacturer: Nutritional Specialties, Inc.
Category: homeopathic | Type: HUMAN OTC DRUG LABEL
Date: 20240924

ACTIVE INGREDIENTS: PETROSELINUM CRISPUM WHOLE 3 [hp_X]/1 mL; SODIUM CHLORIDE 4 [hp_X]/1 mL; BEEF LIVER 6 [hp_X]/1 mL; SUS SCROFA BONE MARROW 6 [hp_X]/1 mL; BOS TAURUS SPLEEN 6 [hp_X]/1 mL; LAMB 6 [hp_X]/1 mL; SACCHARIN 50 [hp_X]/1 mL
INACTIVE INGREDIENTS: WATER; ALCOHOL

DRUG FACTS:

ACTIVE INGREDIENTS:

(in each spray) Hepar (Liver) 6X, 12X, 30X, 100X, Medulla Ossis Suis 6X, 12X, 30X, 100X, Natrum Muriaticum 4X, Petroselinum Sativum 3X, Saccharinum 50X, Spleen 6X, 12X, 30X, 100X, Thymus 6X, 12X, 30X, 100X.

PURPOSE:

Hepar (Liver) – Support of Liver,† Medulla Ossis Suis – Relief of Achiness,† Natrum Muriaticum – Assists in Relieving Sinus Symptoms, Minor Breathing Issues, Achiness and Fever,† Petroselinum Sativum – Assists in Relieving Fever,† Saccharinum – Assists in Relieving Achiness and Fever,† Spleen – Support of Spleen,† Thymus – Support of Thymus†

USES:

To aid in the temporary relief of symptoms associated with viral infections, such as achiness and fever.

†Claims based on traditional homeopathic practice, not accepted medical evidence. Not FDA evaluated.

WARNINGS:

If pregnant or breast-feeding, ask a health professional before use.

In case of overdose, get medical help or contact a Poison Control Center right away.

If condition worsens, seek medical attention.

KEEP OUT OF REACH OF CHILDREN

Do not use if tamper evident seal is broken or missing.

Store in a cool place after opening

KEEP OUT OF REACH OF CHILDREN:

In case of overdose, get medical help or contact a Poison Control Center right away.

DIRECTIONS:

• Adults: 2 to 3 sprays orally, three times daily. Children under twelve one half adult dosage.

• Do not take within 15 minutes of consuming food, beverage or brushing teeth.

Consult a physician for use in children under 12 years of age.

INACTIVE INGREDIENTS:

Alcohol USP 20%, Purified Water USP.

QUESTIONS:

MANUFACTURED EXCLUSIVELY FOR

NUTRITIONAL SPECIALTIES, INC.

PO BOX 97227

PITTSBURG, PA 15229

www.phpltd.com

1-800-245-1313

PACKAGE LABEL DISPLAY:

Professional

Health Products

HOMEOPATHIC

NDC 83027-0145-1

DEFENSE

2 FL. OZ (60 ml)